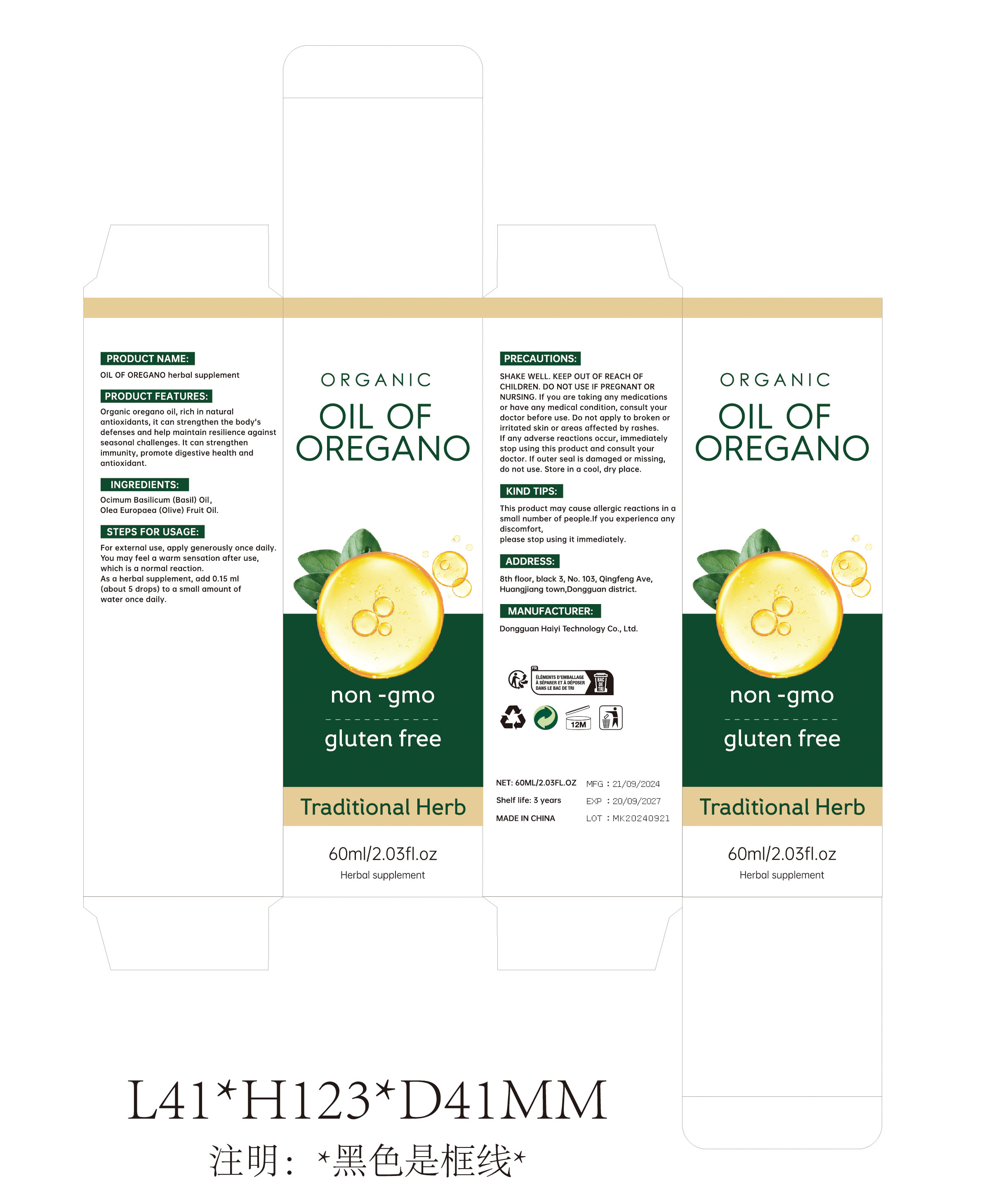 DRUG LABEL: Oregano Oil Herbal Blend
NDC: 84732-029 | Form: OIL
Manufacturer: Dongguan Haiyi Technology Co.,Ltd.
Category: otc | Type: HUMAN OTC DRUG LABEL
Date: 20240930

ACTIVE INGREDIENTS: BASIL OIL 1 mg/60 mL
INACTIVE INGREDIENTS: OLIVE OIL

Active ingredient

Ocimum Basilicum (Basil) Oil

Inactive ingredient

Olea Europaea (Olive) Fruit Oil

Purpose section

Organic oregano oil, rich in natural antioxidants, it can strengthen the body'sdefenses and help maintain resilience against seasonal challenges.lt can strengthen immunity, promote digestive health and antioxidant.

Warning

SHAKE WELL. KEEP OUT OF REACH OFCHILDREN. DO NOT USE IF PREGNANT ORNURSING.

If you are taking any medicationsor have any medical condition, consult yourdoctor before use. Do not apply to broken orirritated skin or areas affected by rashes.If any adverse reactions occur, immediatelystop using this product and consult yourdoctor.lf outer seal is damaged or missing,do not use. Store in a cool, dry place.

stop use

This product may cause allergic reactions in asmall number of people.
lf youexperience any discomfort,please stop using it immediately.

not use

Not suitable for use by children, pregnantor breast feeding people.

OUT OF CHILDREN

KEEP THE PRODUCT OUT OF REACH OF CHILDREN to

HOW TO USE

For external use, apply generously once dailyYou may feel a warm sensation after use,which is a normal reaction.As a herbal supplement, add 0.15 ml(about 5 drops) to a small amount of water once daily.

DOSAGE

As a herbal supplement, add 0.15 ml(about 5 drops) to a small amount of water once daily.